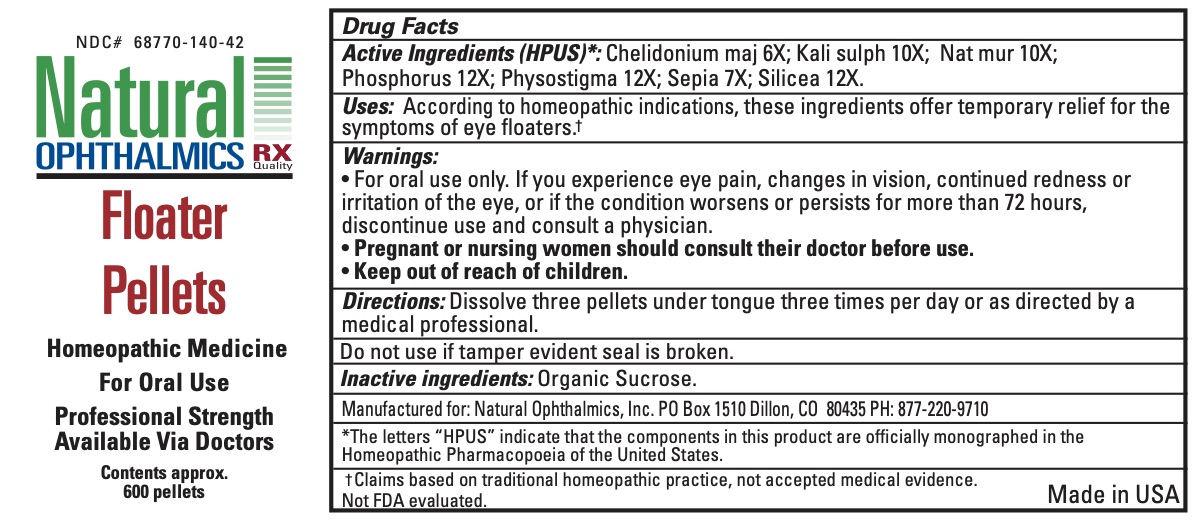 DRUG LABEL: Floater
NDC: 68770-140 | Form: PELLET
Manufacturer: Natural Ophthalmics, Inc
Category: homeopathic | Type: HUMAN OTC DRUG LABEL
Date: 20231231

ACTIVE INGREDIENTS: SILICON DIOXIDE 12 [hp_X]/1 1; SODIUM CHLORIDE 10 [hp_X]/1 1; CHELIDONIUM MAJUS WHOLE 6 [hp_X]/1 1; PHYSOSTIGMA VENENOSUM SEED 12 [hp_X]/1 1; SEPIA OFFICINALIS JUICE 7 [hp_X]/1 1; POTASSIUM SULFATE 10 [hp_X]/1 1; PHOSPHORUS 12 [hp_X]/1 1
INACTIVE INGREDIENTS: SUCROSE

Floater Pellets

ACTIVE INGREDIENT

Active Ingredients (HPUS)*: Chelidonium maj 6X; Kali sulph 10X; Nat mur 10X; Phosphorus 12X; Physostigma 12X; Sepia 7X; Silicea 12X.

INDICATIONS AND USAGE

Uses: According to homeopathic indications, these ingredients offer temporary relief for the symptoms of eye floaters.†

Warnings:

• For oral use only. If you experience eye pain, changes in vision, continued redness or irritation of the eye, or if the condition worsens or persists for more than 72 hours, discontinue use and consult a physician.

PREGNANCY OR BREAST FEEDING

Pregnant or nursing women should consult their doctor before use.

Keep out of reach of children

INACTIVE INGREDIENT

organic sucrose

Directions:

Dissolve three pellets under tongue three times per day or as directed by a medical professional.

Do not use if tamper evident seal is broken.

*The letters “HPUS” indicate that the components in this product are officially monographed in the Homeopathic Pharmacopoeia of the United States.

† Claims based on traditional homeopathic practice, not accepted medical evidence.
Not FDA evaluated.

Manufactured for: Natural Ophthalmics, Inc. PO Box 1510 Dillon, CO 80435 PH: 877-220-9710